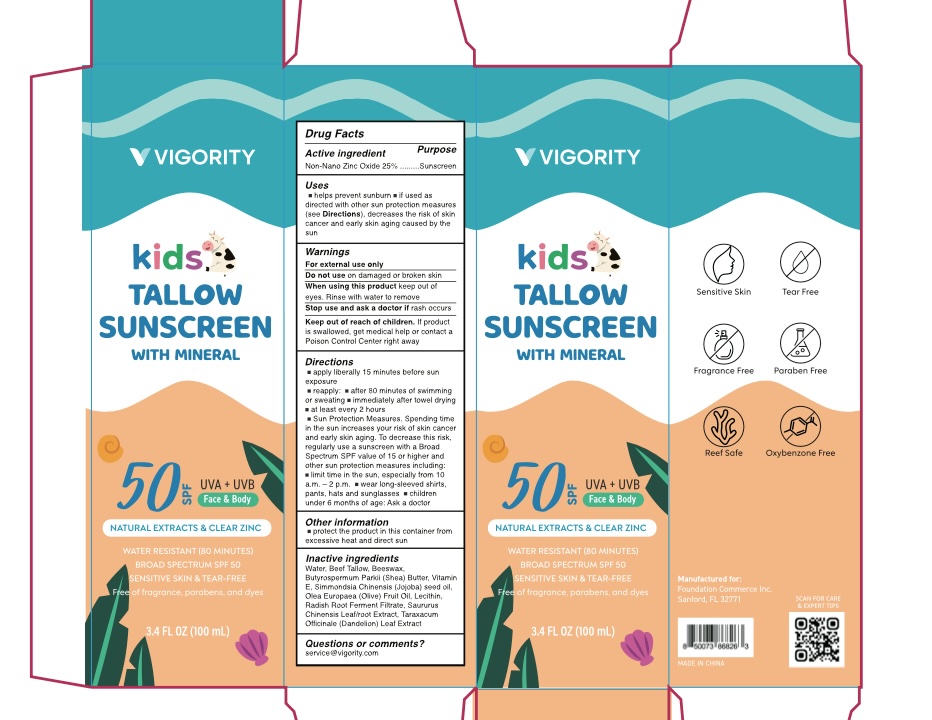 DRUG LABEL: Kids Tallow Sunscreen SPF50
NDC: 85739-005 | Form: CREAM
Manufacturer: FOUNDATION COMMERCE INC
Category: otc | Type: HUMAN OTC DRUG LABEL
Date: 20250801

ACTIVE INGREDIENTS: ZINC OXIDE 25 g/100 mL
INACTIVE INGREDIENTS: BUTYROSPERMUM PARKII (SHEA) BUTTER; WATER; BEESWAX; SIMMONDSIA CHINENSIS (JOJOBA) SEED OIL; OLEA EUROPAEA (OLIVE) FRUIT OIL; LECITHIN, SOYBEAN; LEUCONOSTOC/RADISH ROOT FERMENT FILTRATE; SAURURUS CHINENSIS WHOLE; BEEF TALLOW; TARAXACUM OFFICINALE LEAF; TOCOPHEROL

Initial Drug Listing - Vigority Kids Tallow Sunscreen SPF50

ACTIVE INGREDIENT

Non-Nano Zinc Oxide 25%

PURPOSE

Sunscreen

INDICATIONS AND USAGE

- helps prevent sunburn.
- if used as directed with other sun protection measures (see directions), decrease the risk of skin cancer and early skin aging caused b the sun.

WARNINGS

For external use only

Do not use on damaged or broken skin.

When using this product keep out of eyes. Rinse with water to remove.

Stop use and ask a doctor if rash occurs.

Keep out of reach of children. If product is swallowed, get medical help or contact a Poison Control Center right away.

DOSAGE AND ADMINISTRATION

- apply liberally 15 minutes before sun exposure
- reapply: - after 80 minutes of swimming or sweating - immediately after towel drying
- at least every 2 hours
- Sun Protection Measures. Spending time in the sun increases your risk of skin cancer and early skin aging. To decrease this risk, regularly use a sunscreen with a Broad Spectrum SPF value of 15 or higher and other sun protection measures including:
- limit time in the sun, especially from 10 a.m. - 2 p.m. - wear long-sleeved shirts, pants, hats and sunglasses - children under 6 months of age: Ask a doctor

OTHER SAFETY INFORMATION

Protect the product in this container from excessive heat and direct sun.

INACTIVE INGREDIENT

Water, Beef Tallow, Beeswax, Butyrospermum Parkii (Shea) Butter, Tocopherol, Simmondsia Chinensis (Jojoba) seed oil, Olea Europaea (Olive) Fruit Oil, Lecithin, Radish Root Ferment Filtrate, Saururus Chinensis Leaf/root Extract, Taraxacum Officinale (Dandelion) Leaf Extract

QUESTIONS

service@vigority.com